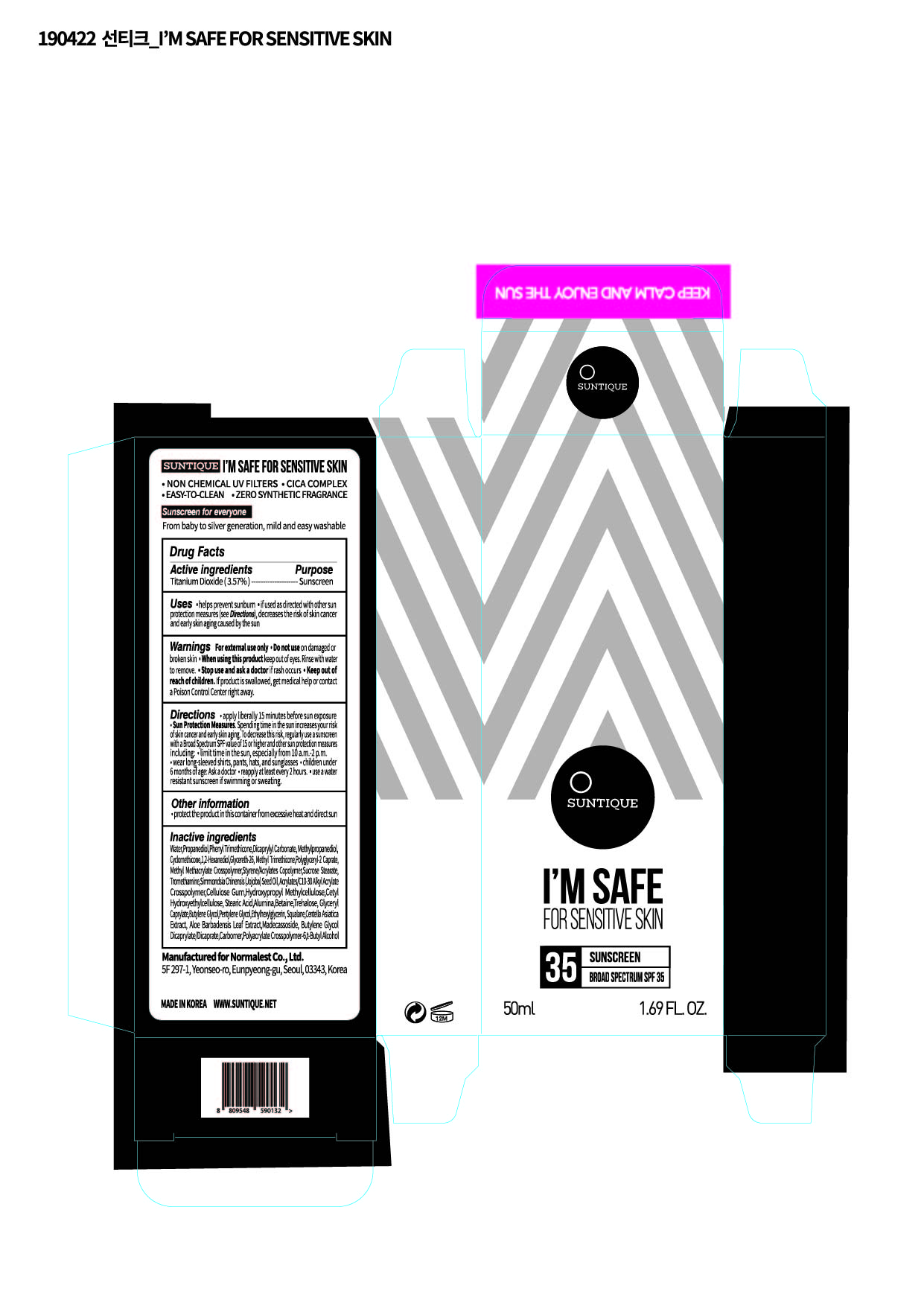 DRUG LABEL: IM SAFE FOR SENSITIVE SKIN
NDC: 72284-0007 | Form: LOTION
Manufacturer: Normalest Co., Ltd.
Category: otc | Type: HUMAN OTC DRUG LABEL
Date: 20190423

ACTIVE INGREDIENTS: TITANIUM DIOXIDE 1.785 g/50 mL
INACTIVE INGREDIENTS: SUCROSE STEARATE; BETAINE; TREHALOSE; GLYCERYL CAPRYLATE; PENTYLENE GLYCOL; ETHYLHEXYLGLYCERIN; SQUALANE; CENTELLA ASIATICA; AMMONIUM ACRYLOYLDIMETHYLTAURATE, DIMETHYLACRYLAMIDE, LAURYL METHACRYLATE AND LAURETH-4 METHACRYLATE COPOLYMER, TRIMETHYLOLPROPANE TRIACRYLATE CROSSLINKED (45000 MPA.S); TERT-BUTYL ALCOHOL; WATER; DICAPRYLYL CARBONATE; 1,2-HEXANEDIOL; PROPANEDIOL; PHENYL TRIMETHICONE; METHYLPROPANEDIOL; METHYL TRIMETHICONE; JOJOBA OIL; TROMETHAMINE; BUTYLENE GLYCOL; ALOE VERA LEAF; MADECASSOSIDE; BUTYLENE GLYCOL DICAPRYLATE/DICAPRATE; CARBOXYMETHYLCELLULOSE SODIUM; HYPROMELLOSES; STEARIC ACID; ALUMINUM OXIDE; GLYCERETH-26; METHYL METHACRYLATE/GLYCOL DIMETHACRYLATE CROSSPOLYMER

PACKAGE LABEL

Active Ingredients

Titanium Dioxide

Inactive Ingredients

Water, Propanediol, Phenyl Trimethicone, Dicaprylyl Carbonate, Methylpropanediol, Cyclopentasiloxane,1,2-Hexanediol, Glycereth-26, Methyl Trimethicone, Polyglyceryl-2 Caprate, Methyl Methacrylate Crosspolymer, Styrene/Acrylates Copolymer ,Sucrose Stearate, Tromethamine, Simmondsia Chinensis (Jojoba) Seed Oil, Acrylates/C10-30 Alkyl Acrylate Crosspolymer, Cellulose Gum, Hydroxypropyl Methylcellulose, Cetyl Hydroxyethylcellulose, Stearic Acid, Alumina, Betaine, Trehalose, Glyceryl Caprylate, Butylene Glycol, Pentylene Glycol, Ethylhexylglycerin, Squalane, Centella Asiatica Extract, Aloe Barbadensis Leaf Extract, Madecassoside, Butylene Glycol Dicaprylate/Dicaprate, Carbomer, Polyacrylate Crosspolymer-6, t-Butyl Alcohol